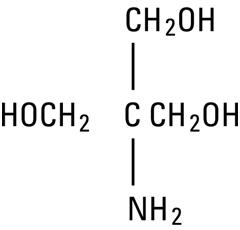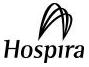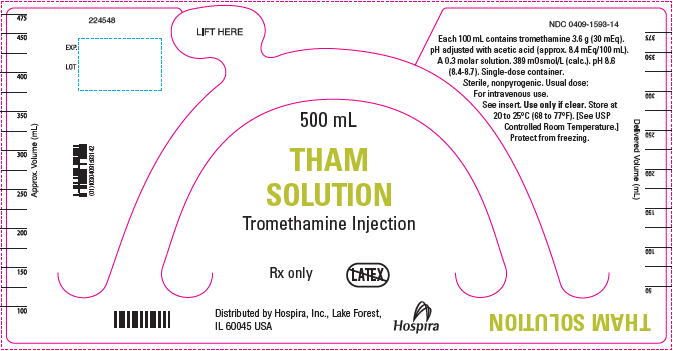 DRUG LABEL: THAM
NDC: 0409-1593 | Form: INJECTION, SOLUTION
Manufacturer: Hospira, Inc.
Category: prescription | Type: HUMAN PRESCRIPTION DRUG LABEL
Date: 20241213

ACTIVE INGREDIENTS: TROMETHAMINE 3.6 g/100 mL
INACTIVE INGREDIENTS: WATER; ACETIC ACID

THAM SOLUTION
Tromethamine Injection

For the Prevention and Correction of Severe Metabolic Acidosis

Large Volume Glass Container

Rx only

DESCRIPTION

Tham Solution (tromethamine injection) is a sterile, non-pyrogenic 0.3 M solution of tromethamine, adjusted to a pH of approximately 8.6 with glacial acetic acid. It is administered by intravenous injection, by addition to ACD blood for priming cardiac bypass equipment and by injection into the ventricular cavity during cardiac arrest.

Each 100 mL contains tromethamine 3.6 g (30 mEq) in water for injection. The solution is hypertonic 389 mOsmol/L (calc.). pH 8.6 (8.4-8.7).

The solution contains no bacteriostat, antimicrobial agent or added buffer (except acetic acid for pH adjustment) and is intended only for use as a single-dose injection. When smaller doses are required the unused portion should be discarded.

Tham solution is a parenteral systemic alkalizer and fluid replenisher.

Tromethamine, USP (sometimes called “tris” or “tris buffer”) is chemically designated 2-amino-2-(hydroxymethyl)-1, 3-propanediol, a solid readily soluble in water, also classified as an organic amine buffer. It has the following structural formula:

Water for Injection, USP is chemically designated H20.

CLINICAL PHARMACOLOGY

When administered intravenously as a 0.3 M solution, tromethamine act as a proton acceptor and prevents or corrects acidosis by actively binding hydrogen ions (H^+). It binds not only cations of fixed or metabolic acids, but also hydrogen ions of carbonic acid, thus increasing bicarbonate anion (HCO3‾). Tromethamine also acts as an osmotic diuretic, increasing urine flow, urinary pH, and excretion of fixed acids, carbon dioxide and electrolytes. A significant fraction of tromethamine (30% at pH 7.40) is not ionized and therefore is capable of reaching equilibrium in total body water. This portion may penetrate cells and may neutralize acidic ions of the intracellular fluid.

The drug is rapidly eliminated by the kidney; 75% or more appears in the urine after eight hours. Urinary excretion continues over a period of three days.

Water is an essential constituent of all body tissues and accounts for approximately 70% of total body weight. Average normal adult daily requirement ranges from two to three liters (1.0 to 1.5 liters each for insensible water loss by perspiration and urine production).

Water balance is maintained by various regulatory mechanisms. Water distribution depends primarily on the concentration of electrolytes in the body compartments and sodium (Na^+) plays a major role in maintaining physiologic equilibrium.

INDICATIONS AND USAGE

Tham Solution (tromethamine injection) is indicated for the prevention and correction of metabolic acidosis. In the following conditions it may help to sustain vital functions and thus provide time for treatment of the primary disease:

Metabolic Acidosis Associated with Cardiac Bypass Surgery.
Tham Solution has been found to be primarily beneficial in correcting metabolic acidosis which may occur during or immediately following cardiac bypass surgical procedures.
Correction of Acidity of ACD Blood in Cardiac Bypass Surgery.
It is well known that ACD blood is acidic and becomes more acidic on storage. Tromethamine effectively corrects this acidity. Tham Solution may be added directly to the blood used to prime the pump-oxygenator. When ACD blood is brought to a normal pH range the patient is spared an initial acid load. Additional tromethamine may be indicated during cardiac bypass surgery should metabolic acidosis appear.
Metabolic Acidosis Associated with Cardiac Arrest.
Acidosis is nearly always one of the consequences of cardiac arrest and, in some instances, may even be a causative factor in arrest. It is important therefore, that the correction of acidosis should be started promptly with other resuscitative efforts. By correcting acidosis, Tham Solution (tromethamine injection) has caused the arrested heart to respond to resuscitative efforts after standard methods alone had failed. In these cases, tromethamine was given intraventricularly. It is to be noted, however, that such precariously ill patients often have died subsequently of causes unrelated to the administration of tromethamine. With administration by the peripheral venous route, metabolic acidosis has been corrected in a majority of patients. The success in reinstitution of cardiac rhythm by this means probably has not been of the same order of magnitude as with the intraventricular route.

CONTRAINDICATIONS

Tham Solution (tromethamine injection) is contraindicated in uremia and anuria. In neonates it is also contraindicated in chronic respiratory acidosis and salicylate intoxication.

WARNINGS

Large doses of Tham Solution may depress ventilation, as a result of increased blood pH and reduced CO2 concentration. Thus, dosage should be adjusted so that blood pH is not allowed to increase above normal. In situations in which respiratory acidosis may be present concomitantly with metabolic acidosis, the drug may be used with mechanical assistance to ventilation.
Care must be exercised to prevent perivascular infiltration since this can cause inflammation, necrosis and sloughing of tissue. Venospasm and intravenous thrombosis, which may occur during infusion, can be minimized by insuring that the injection needle is well within the largest available vein and that solutions are slowly infused. Intravenous catheters are recommended. If perivascular infiltration occurs, institute appropriate countermeasures (see ADVERSE REACTIONS).
Tham Solution (tromethamine injection) should be administered slowly and in amounts sufficient only to correct the existing acidosis, and to avoid overdosage and alkalosis. Overdosage in terms of total drug and/or too rapid administration, may cause hypoglycemia of a prolonged duration (several hours). Therefore, frequent blood glucose determinations should be made during and after therapy.
Extreme care should be exercised in patients with renal disease or reduced urinary output because of potential hyperkalemia and the possibility of a decreased excretion of tromethamine. In such patients, the drug should be used cautiously with electrocardiographic monitoring and frequent serum potassium determinations.
Because clinical experience has been limited generally to short-term use, the drug should not be administered for more than a period of one day except in a life-threatening situation.

The intravenous administration of Tham Solution can cause fluid and/or solute overloading resulting in dilution of serum electrolyte concentrations, overhydration, congested states or pulmonary edema.

Additives may be incompatible. Consult with pharmacist, if available. When introducing additives, use aseptic technique, mix thoroughly and do not store.

PRECAUTIONS

Blood pH, PCO2 bicarbonate, glucose and electrolyte determinations should be performed before, during and after administration of Tham Solution.
While it has not been shown that the drug increases coagulation time in humans, this possibility should be kept in mind since this has been noted experimentally in dogs.

Do not administer unless solution is clear and seal is intact. Discard unused portion.

Pregnancy:

Animal reproduction studies have not been conducted with tromethamine. It is also not known whether tromethamine can cause fetal harm when administered to a pregnant woman or can affect reproduction capacity. Tromethamine should be given to a pregnant woman only if clearly needed.

Nursing Mothers:

It is not known whether this drug is excreted in human milk. Because many drugs are excreted in human milk, caution should be exercised when THAM Solution is administered to a nursing mother.

Carcinogenesis, Mutagenesis, Impairment of Fertility:

Studies with THAM Solution have not been performed to evaluate carcinogenic potential, mutagenic potential or effects on fertility.

Pediatric Use:

The safety and effectiveness of THAM Solution in pediatric patients is based on over 30 years’ clinical experience documented in the literature and on safety surveillance. THAM Solution has been used to treat severe cases of metabolic acidosis with concurrent respiratory acidosis because it does not raise PCO2 as bicarbonate does in neonates and infants with respiratory failure. It has also been used in neonates and infants with hypernatremia and metabolic acidosis to avoid the additional sodium given with the bicarbonate. However, because the osmotic effects of THAM Solution are greater and large continuous doses are required, bicarbonate is preferred to THAM Solution in the treatment of acidotic neonates and infants with RDS. Hypoglycemia may occur when this product is used in premature and even full-term neonates (see WARNINGS and ADVERSE REACTIONS).

Geriatric Use:

Clinical studies of Tham solution did not include sufficient numbers of subjects aged 65 and over to determine whether they respond differently from younger subjects. Other reported clinical experience has not identified differences in response between the elderly and younger patients. In general, dose selection for an elderly patient should be cautious, usually starting at the low end of the dosing range, reflecting the greater frequency of decreased hepatic, renal, or cardiac function, and of concomitant disease or other drug therapy.

This drug is known to be substantially excreted by the kidney, and the risk of toxic reactions to this drug may be greater in patients with impaired renal function. Because elderly patients are more likely to have decreased renal function, care should be taken in dose selection, and it may be useful to monitor renal function.

ADVERSE REACTIONS

Generally, side effects have been infrequent.

Respiratory: Although the incidence of ventilatory depression is low, it is important to keep in mind that such depression may occur. Respiratory depression may be more likely to occur in patients who have chronic hypoventilation or those who have been treated with drugs which depress respiration. In patients with associated respiratory acidosis, tromethamine should be administered with mechanical assistance to ventilation.

Vascular: Extreme care should be taken to avoid perivascular infiltration. Local tissue damage and subsequent sloughing may occur if extravasation occurs. Chemical phlebitis and venospasm also have been reported.

Hematologic: Transient depression of blood glucose may occur.

Hepatic: Infusion via low-lying umbilical venous catheters has been associated with hepatocellular necrosis.

Reactions which may occur because of the solution or the technique of administration include febrile response, infection at the site of injection, venous thrombosis or phlebitis extending from the site of injection extravasation and hypervolemia.

If an adverse reaction does occur, discontinue the infusion, evaluate the patient, institute appropriate therapeutic countermeasures and save the remainder of the fluid for examination if deemed necessary.

OVERDOSAGE

Too rapid administration and/or excessive amounts of tromethamine may cause alkalosis, hypoglycemia, overhydration or solute overload. In the event of overdosage, discontinue the infusion, evaluate the patient and institute appropriate countermeasures (see WARNINGS, PRECAUTIONS and ADVERSE REACTIONS).

The LD50 values for the acute intravenous toxicity of THAM are influenced by the rate of infusion of the dose administered.

Intravenous LD50 Mice = 3,500 mg/kg

Intravenous LD50 Rats = 2,300 mg/kg

DOSAGE AND ADMINISTRATION

Tham Solution (tromethamine injection) is administered by slow intravenous infusion, by addition to pump-oxygenator ACD blood or other priming fluid or by injection into the ventricular cavity during cardiac arrest. For infusion by peripheral vein, a large needle should be used in the largest antecubital vein or an indwelling catheter placed in a large vein of an elevated limb to minimize chemical irritation of the alkaline solution during infusion. Catheters are recommended.

Dosage and rate of administration should be carefully supervised to avoid overtreatment (alkalosis). Pretreatment and subsequent determinations of blood values (e.g. pH, PCO2, PO2, glucose and electrolytes) and urinary output should be made as necessary to monitor dosage and progress of treatment. In general, dosage should be limited to an amount sufficient to increase blood pH to normal limits (7.35 to 7.45) and to correct acid-base derangements. The total quantity to be administered during the period of illness will depend upon the severity and progression of the acidosis. The possibility of some retention of tromethamine, especially in patients with impaired renal function, should be kept in mind.

The intravenous dosage of Tham Solution (tromethamine injection) may be estimated from the buffer base deficit of the extracellular fluid in mEq/liter determined by means of the Siggaard-Andersen nomogram. The following formula is intended as a general guide:

Tham Solution (mL of 0.3 M) Required =

Body Weight (kg) X

Base Deficit (mEq/liter) X 1.1*

Thus, a 70 kg patient with a buffer base deficit (“negative base excess”) of 5 mEq/liter would require 70 x 5 x 1.1 = 385 mL of Tham Solution containing 13.9 g (115 mEq) of tromethamine. The need for administration of additional Tham Solution is determined by serial determinations of the existing base deficit.

* Factor of 1.1 accounts for an approximate reduction of 10% in buffering capacity due to the presence of sufficient acetic acid to lower pH of the 0.3 M solution to approximately 8.6.

Correction of Metabolic Acidosis Associated with Cardiac Bypass Surgery: An adverse dose of approximately 9.0 mL/kg (324 mg/kg) has been used in clinical studies with Tham Solution (tromethamine injection). This is equivalent to a total dose of 630 mL (189 mEq) for 70 kg patient. A total single dose of 500 mL (150 mEq) is considered adequate for most adults. Larger single doses (up to 1000 mL) may be required in unusually severe cases.

It is recommended that individual doses should not exceed 500 mg/kg (227 mg/lb) over a period of not less than one hour. Thus, for a 70 kg (154 pound) patient the dose should not exceed a maximum of 35 g per hour (1078 mL of a 0.3 M solution). Repeated determinations of pH and other clinical observations should be used as a guide to the need for repeat doses.

Correction of Acidity of ACD Blood in Cardiac Bypass Surgery: The pH of stored blood ranges from 6.80 to 6.22 depending upon the duration of storage. The amount of Tham Solution used to correct this acidity ranges from 0.5 to 2.5 g (15 to 77 mL of a 0.3 M solution) added to each 500 mL of ACD blood used for priming the pump-oxygenator. Clinical experience indicates that 2 g (62 mL of a 0.3 M solution) added to 500 mL of ACD blood is usually adequate.

Correction of Metabolic Acidosis Associated with Cardiac Arrest: In the treatment of cardiac arrest, Tham Solution should be given at the same time that other standard resuscitative measures, including manual systole, are being applied. If the chest is open, Tham Solution is injected directly into the ventricular cavity. From 2 to 6 g (62 to 185 mL of a 0.3 M solution) should be injected immediately. Do not inject into the cardiac muscle.

If the chest is not open, from 3.6 to 10.8 g (111 to 333 mL of a 0.3 M solution) should be injected immediately into a larger peripheral vein. Additional amounts may be required to control acidosis persisting after cardiac arrest is reversed.

Correction of Metabolic Acidosis Associated with RDS in Neonates and Infants: The initial dose of Tham Solution should be based on initial pH and birthweight amounting to approximately 1 mL per kg for each pH unit below 7.4. Further doses have been given according to changes in PaO2, pH and PCO2.

Parenteral drug products should be inspected visually for particulate matter and discoloration prior to administration, whenever solution and container permit (see CONTRAINDICATIONS).

HOW SUPPLIED

Tham Solution (tromethamine injection) is available as:

Unit of Sale | Concentration
NDC-0409-1593-04 Case of 6 Single-dose 500 mL large volume glass containers | 500 mL (150 mEq)

Store at 20 to 25°C (68 to 77°F). [See USP Controlled Room Temperature.]

Protect from freezing.

Distributed by Hospira, Inc., Lake Forest, IL 60045 USA

LAB-1213-2.0

Revised: 2/2020

PRINCIPAL DISPLAY PANEL - 500 mL Bottle Label

500 mL

THAM
SOLUTION
Tromethamine Injection

Rx only

Distributed by Hospira, Inc., Lake Forest,
IL 60045 USA

Hospira